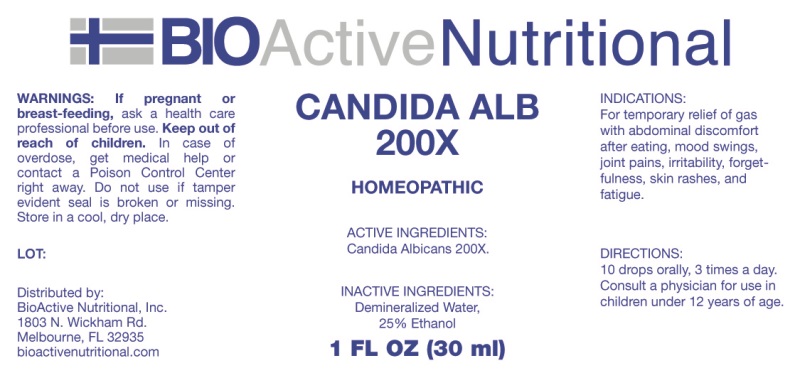 DRUG LABEL: Candida Alb
NDC: 43857-0251 | Form: LIQUID
Manufacturer: BioActive Nutritional, Inc.
Category: homeopathic | Type: HUMAN OTC DRUG LABEL
Date: 20241017

ACTIVE INGREDIENTS: CANDIDA ALBICANS 200 [hp_X]/1 mL
INACTIVE INGREDIENTS: WATER; ALCOHOL

DRUG FACTS:

ACTIVE INGREDIENTS:

Candida Albicans 200X

INDICATIONS:

For temporary relief of gas with abdominal discomfort after eating, mood swings, joint pains, irritability, forgetfulness, skin rashes, and

fatigue.

WARNINGS:

If pregnant or breast-feeding, ask a health care professional before use.

Keep out of reach of children. In case of overdose, get medical help or contact a Poison Control Center right away.

Do not use if tamper evident seal is broken or missing.

Store in a cool, dry place.

Keep out of reach of children. In case of overdose, get medical help or contact a Poison Control Center right away.

DIRECTIONS:

10 drops orally, 3 times a day. Consult a physician for use in children under 12 years of age.

INDICATIONS:

For temporary relief of gas with abdominal discomfort after eating, mood swings, joint pains, irritability, forgetfulness, skin rashes, and

fatigue.

INACTIVE INGREDIENTS:

Demineralized Water, 25% Ethanol

QUESTIONS:

Distributed by:

BioActive Nutritional, Inc.

1803 N. Wickham Rd.

Melbourne, FL 32935

bioactivenutritional.com

PACKAGE DISPLAY LABEL:

BioActive Nutritional

CANDIDA ALB

200X

Homeopathic

1 FL OZ (30 ml)